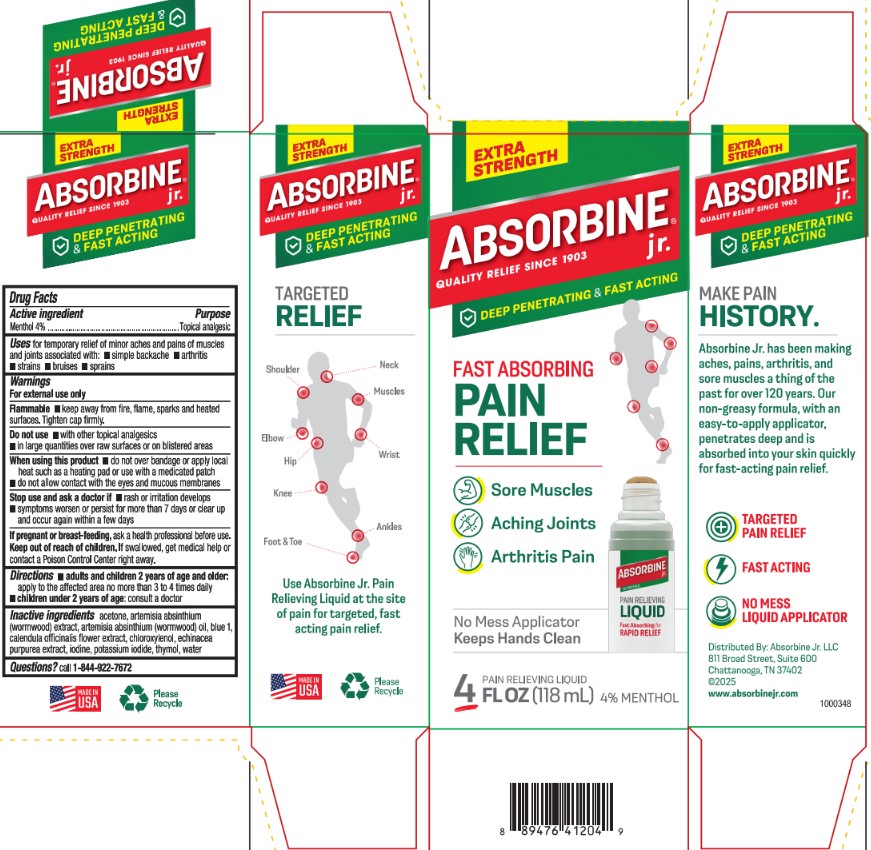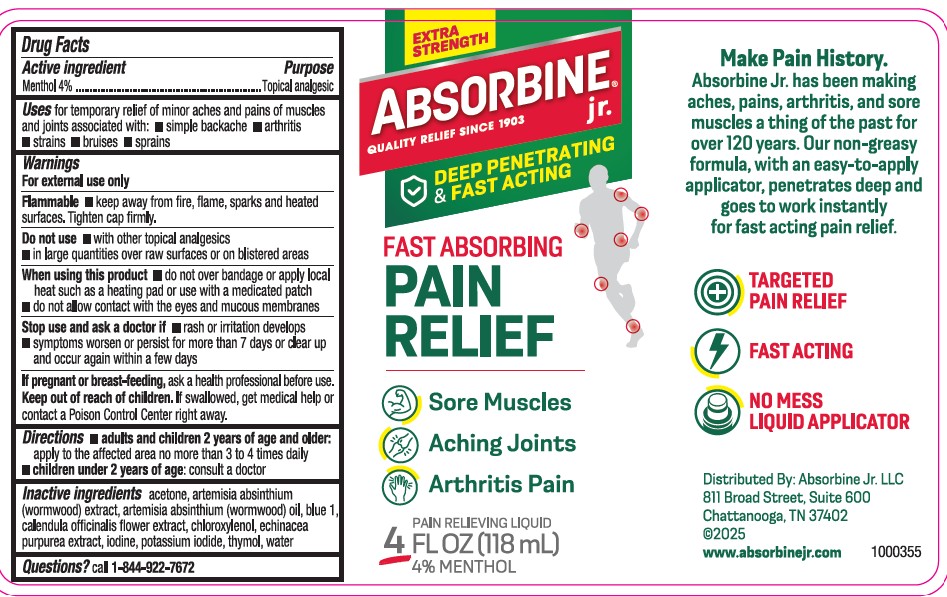 DRUG LABEL: Absorbine Jr. Pro Rollon
NDC: 69693-426 | Form: LIQUID
Manufacturer: Clarion Brands, LLC
Category: otc | Type: HUMAN OTC DRUG LABEL
Date: 20251228

ACTIVE INGREDIENTS: LIDOCAINE 4 g/100 mL; PHENOL 1.5 g/100 mL
INACTIVE INGREDIENTS: WATER

Absorbine jr.®Plus
Drug Facts

Active Ingredient

Menthol 4.0%

Purpose

Topical Analgesic

Uses

For temporary relief of minor aches and pains of muscles and joints associated with:

- arthritis
- simple backache
- sprains
- strains
- bruises

Warnings

For external use only. Use only as directed.

Flammable

- Keep away from fire, flame, sparks and heated surfaces. Tighten cap firmly.

Stop use and ask a doctor if

- Condition worsens or symptoms persist for more than 7 days or clear up and occur again within a few days.

When using this product

- Avoid contact with the eyes
- Do not apply to wounds or damaged skin
- Do not bandage tightly

If pregnant or breast feeding,

ask a health professional before use.

Keep out of reach of children.

If swallowed, get medical help or contact a Poison Control Center right away.

Directions

- adults and children 2 years of age and older: apply to the affected area no more than 3 to 4 times daily
- children under 2 years of age; consult a doctor

Inactive Ingredients

acetone, chloroxylene, FD&C blue #1, Iodine, plant extracts of calendula, echinacea, wormwood herb, potassium iodide, thymol, water, and wormwood oil

Questions?

Call 1-844-922-7672

Principal Display Panel

Extra Strength
ABSORBINE® jr.

QUALITY RELIEF SINCE 1903
DEEP PENETRATING & FAST ACTING
Fast Absorbing Pain Relief
• Sore Muscles

- Aching Joints

• Arthritis Pain

No Mess Applicator Keeps Hands Clean
4 FL OZ (118 ml)4% MENTHOL

MAKE PAIN HISTORY.

Absorbine Jr. has been making aches, pains, arthritis, and sore muscles a thing of the past for over 120 years. Our non-greasy formula, with an easy-to-apply applicator, penetrates deep and is absorbed into your skin quickly for fast-acting pain relief.

TARGETED PAIN RELIEF
FAST ACTING
NO MESS LIQUID APPLICATOR

Distributed by: Absorbine Jr. LLC

811 Broad Street, Suite 600

Chattanooga, TN 37402

©2025

Use Absorbine Jr. Pain Relieving Liquid at the site of pain for targeted, fast acting pain relief.

MADE IN USA

Please recycle

Extra Strength
ABSORBINE® jr.

QUALITY RELIEF SINCE 1903
DEEP PENETRATING & FAST ACTING
Fast Absorbing Pain Relief
• Sore Muscles

Aching Joints

• Arthritis Pain

4 FL OZ (118 ml) 4% MENTHOL

MAKE PAIN HISTORY.

Absorbine Jr. has been making aches, pains, arthritis, and sore muscles a thing of the past for over 120 years. Our non-greasy formula, with an easy-to-apply applicator, penetrates deep and is absorbed into your skin quickly for fast-acting pain relief.

TARGETED PAIN RELIEF
FAST ACTING
NO MESS LIQUID APPLICATOR

Distributed by: Absorbine Jr. LLC

811 Broad Street, Suite 600

Chattanooga, TN 37402

©2025

www.absorbinejr.com 1000355